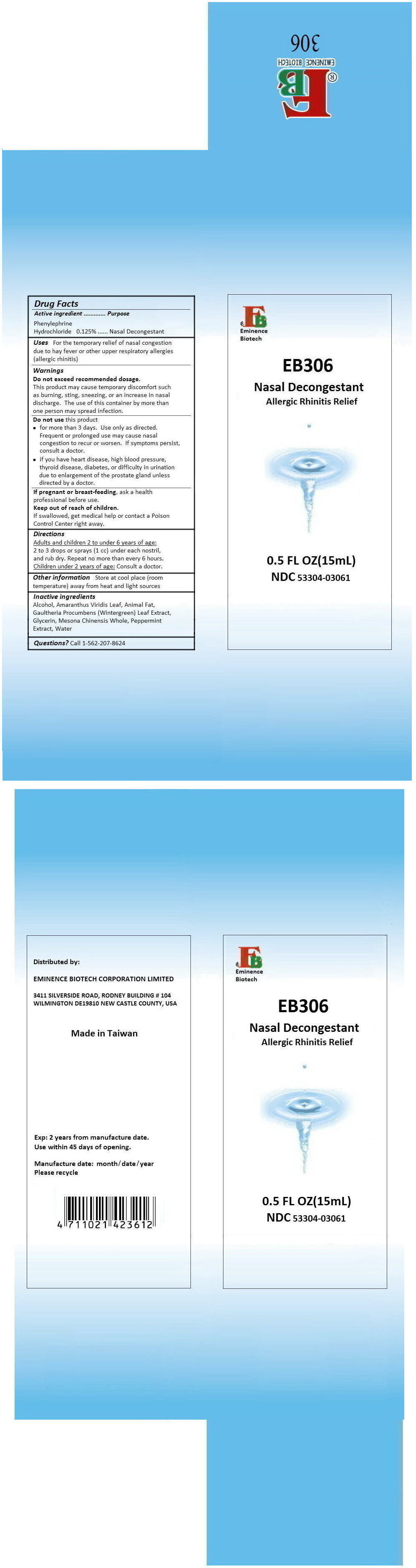 DRUG LABEL: EB306 NASAL DECONGESTANT
NDC: 53304-0306 | Form: SPRAY
Manufacturer: EMINENCE BIOTECH CORPORATION LIMITED
Category: otc | Type: HUMAN OTC DRUG LABEL
Date: 20180320

ACTIVE INGREDIENTS: PHENYLEPHRINE HYDROCHLORIDE 21.73 mg/15 mL
INACTIVE INGREDIENTS: ALCOHOL; AMARANTHUS VIRIDIS LEAF; PORK SIDE BACON, CURED FAT; GAULTHERIA PROCUMBENS LEAF; GLYCERIN; PLATOSTOMA PALUSTRE WHOLE; PEPPERMINT; WATER

EB306 NASAL DECONGESTANT

Drug Facts

Active ingredient

Phenylephrine Hydrochloride 0.125%

Purpose

Nasal Decongestant

Uses

For the temporary relief of nasal congestion due to hay fever or other upper respiratory allergies (allergic rhinitis)

Warnings

Do not exceed recommended dosage.

This product may cause temporary discomfort such as burning, sting, sneezing, or an increase in nasal discharge. The use of this container by more than one person may spread infection.

Do not use this product

- for more than 3 days. Use only as directed. Frequent or prolonged use may cause nasal congestion to recur or worsen. If symptoms persist, consult a doctor.
- if you have heart disease, high blood pressure, thyroid disease, diabetes, or difficulty in urination due to enlargement of the prostate gland unless directed by a doctor.

PREGNANCY OR BREAST FEEDING

If pregnant or breast-feeding, ask a health professional before use.

Keep out of reach of children.

If swallowed, get medical help or contact a Poison Control Center right away.

Directions

Adults and children 2 to under 6 years of age

2 to 3 drops or sprays (1 cc) under each nostril, and rub dry. Repeat no more than every 6 hours.

Children under 2 years of age

Consult a doctor.

Other information

Store at cool place (room temperature) away from heat and light sources

Inactive ingredients

Alcohol, Amaranthus Viridis Leaf, Animal Fat, Gaultheria Procumbens (Wintergreen) Leaf Extract, Glycerin, Mesona Chinensis Whole, Peppermint Extract, Water.

Questions?

Call 1-562-207-8624

Distributed by:

EMINENCE BIOTECH CORPORATION LIMITED

3411 SILVERSIDE ROAD, RODNEY BUILDING #104
WILMINGTON DE19810 NEW CASTLE COUNTY, USA

PRINCIPAL DISPLAY PANEL - 15mL Bottle Carton

EB
Eminence
Biotech

EB306

Nasal Decongestant
Allergic Rhinitis Relief

0.5 FL OZ(15mL)
NDC 53304-03061